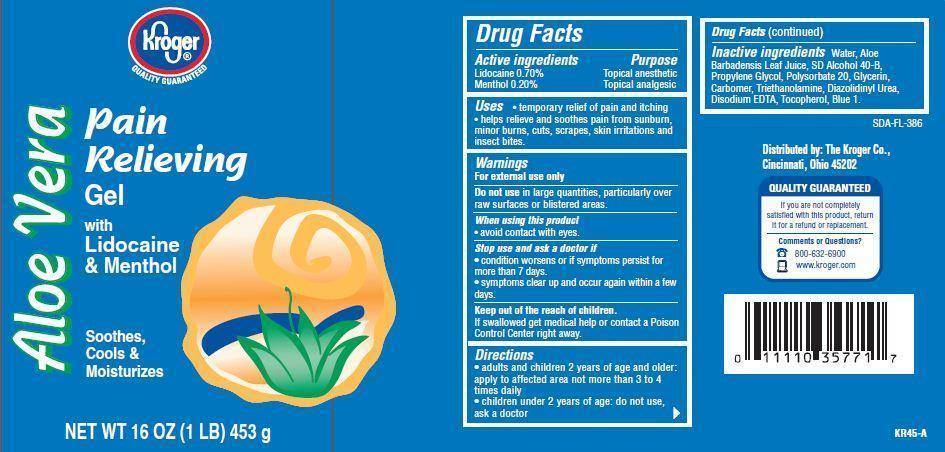 DRUG LABEL: Kroger Aloe Vera
NDC: 30142-905 | Form: LOTION
Manufacturer: THE KROGER CO
Category: otc | Type: HUMAN OTC DRUG LABEL
Date: 20121119

ACTIVE INGREDIENTS: LIDOCAINE 0.7 g/100 g; MENTHOL 0.2 g/100 g
INACTIVE INGREDIENTS: WATER; TROLAMINE; TOCOPHEROL; EDETATE DISODIUM; ALOE VERA LEAF; PROPYLENE GLYCOL; GLYCERIN; POLYSORBATE 20; DIAZOLIDINYL UREA

Drug Facts

Active ingredients

Lidocaine 0.70%
Menthol 0.20%

Purpose

Topical anesthetic
Topical analgesic

Uses

- temporary relief of pain and itching
- helps relieve and soothes pain from sunburn, minor burns, cuts, scrapes, skin irritations and insect bites.

Warnings

For external use only

Do not use in large quantities, particularly over raw surfaces or blistered areas.

When using this product

- avoid contact with eyes.

Stop use and ask a doctor if

- conditions worsens or if symptoms persists for more than 7 days.
- symptoms clear up and occur again within a few days.

Keep out of the reach of children.

If swallowed get medical help or contact a Poison Control Center right away.

Directions

- adults and children 2 years of age and older.apply to affected area not more than 3 to 4 times daily
- children under 2 years of age: do not use, ask a doctor.

Inactive ingredients

Water, Alcohol Denat., Propylene Glycol, Glycerin, Polysorbate 20, Carbomer, Triethanolamine, Aloe Barbadensis Leaf Juice, Disodium EDTA, Tocopherol, Diazolidinyl Urea, Blue 1.

Principal Display Panel

Kroger
QUALITY GURANTEED
Aloe Vera
Pain
Relieving
Gel
with
Lidocaine
and Menthol
Sppthes
Cools and
Moisturizes
NET WT 16 OZ (1 LB) 453 g